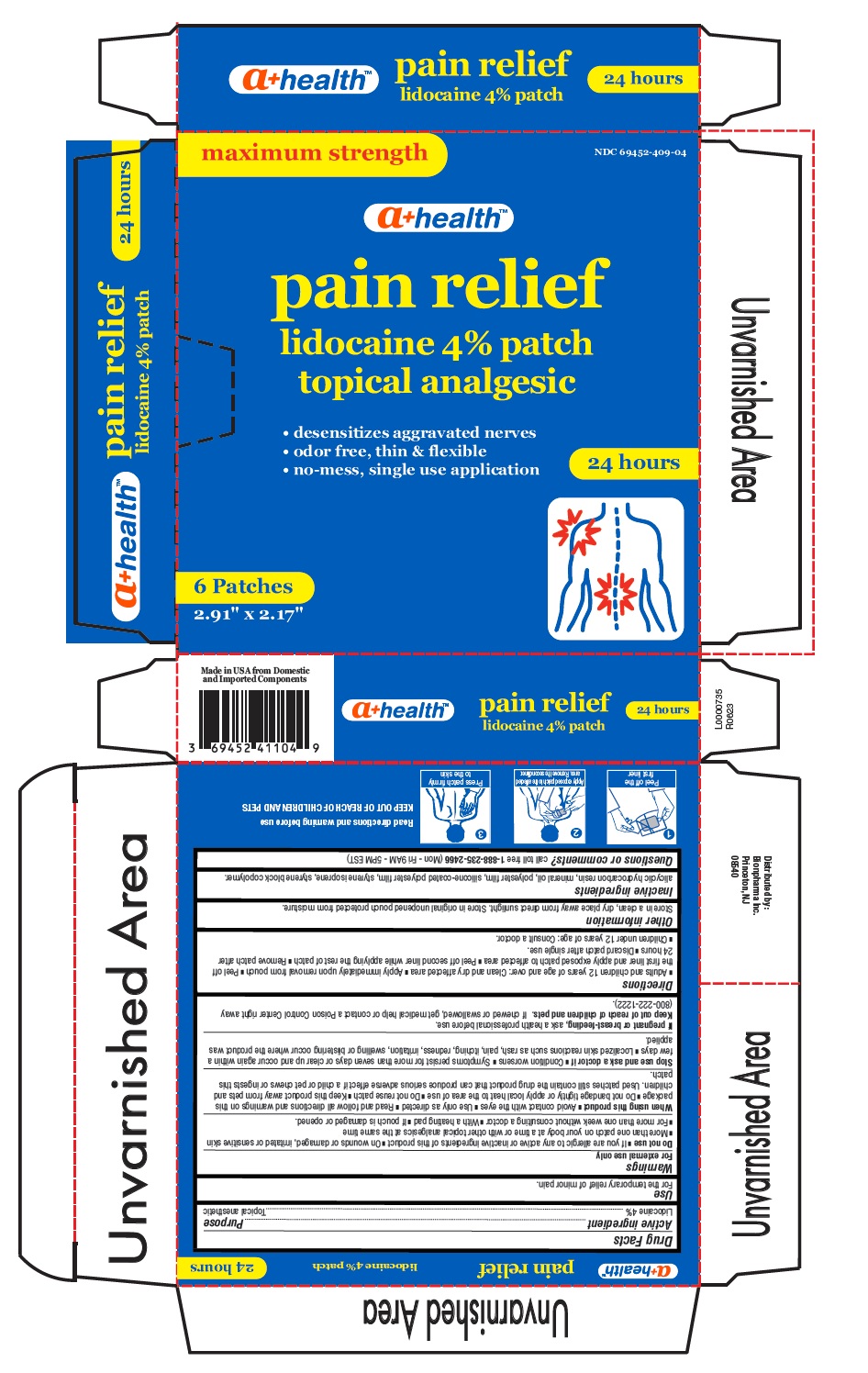 DRUG LABEL: pain relief patch
NDC: 69452-409 | Form: PATCH
Manufacturer: Bionpharma Inc.
Category: otc | Type: HUMAN OTC DRUG LABEL
Date: 20241003

ACTIVE INGREDIENTS: LIDOCAINE 4 g/100 g
INACTIVE INGREDIENTS: HYDROGENATED C6-20 POLYOLEFIN (100 CST); STYRENE/ISOPRENE/STYRENE BLOCK COPOLYMER (STYRENE/ISOPRENE 15/85); MINERAL OIL

Lidocaine 4% pain relief patch

Active ingredient

Lidocaine 4%

Purpose

Topical anesthetic

Uses

For the temporary relief of minor pain.

Warnings

For external use only.

Do not use

■ If you are allergic to any active or inactive ingredients of this product ■ On wounds or damaged, irritated or sensitive skin
■ More than one patch on your body at a time or with other topical analgesics at the same time
■ For more than one week without consulting a doctor ■ With a heating pad ■ If pouch is damaged or opened.

When using this product

■ Avoid contact with the eyes ■ Use only as directed ■ Read and follow all directions and warnings on this
package ■ Do not bandage tightly or apply local heat to the area of use ■ Do not reuse patch ■ Keep this product away from pets and
children. Used patches still contain the drug product that can produce serious adverse effect if a child or pet chews or ingests this
patch

Stop use and ask a doctor if

■ Condition worsens ■ Symptoms persist for more than seven days or clear up and occur again within a
few days ■ Localized skin reactions such as rash, pain, itching, redness, irritation, swelling or blistering occur where the product was
applied.

If pregnant or breast-feeding,

ask a health professional before use.

Keep out of reach of children and pets

If chewed or swallowed, get medical help or contact a Poison Control Center right away (800-222-1222).

Directions

■ Adults and children 12 years of age and over: Clean and dry affected area ■ Apply immediately upon removal from pouch ■ Peel off
the first liner and apply exposed patch to affected area ■ Peel off second liner while applying the rest of patch ■ Remove patch after
24 hours ■ Discard patch after single use.
■ Children under 12 years of age: Consult a doctor.

Other information

Store in a clean, dry place away from direct sunlight. Store in original unopened pouch protected from moisture.

Inactive ingredients

alicyclic hydrocarbon resin, mineral oil, polyester film, silicone-coated polyester film, styrene isoprene, styrene block copolymer.

Questions or comments?

call toll free 1-888-235-2466 (Mon - Fri 9AM - 5PM EST)

Read directions and warning before use

KEEP OUT OF REACH OF CHILDREN AND PETS

Made in USA from Domestic and Imported Components

Distributed by:
Bionpharma Inc.
Princeton, NJ
08540

L0000735
R0623

Carton Label

NDC 69452-409-04

maximum strength

a+ healthTM

pain relief
lidocaine 4% patch
topical analgesic

• desensitizes aggravated nerves
• odor free, thin & flexible
• no-mess, single use application

24 hours

6 Patches

2.91" x 2.17"